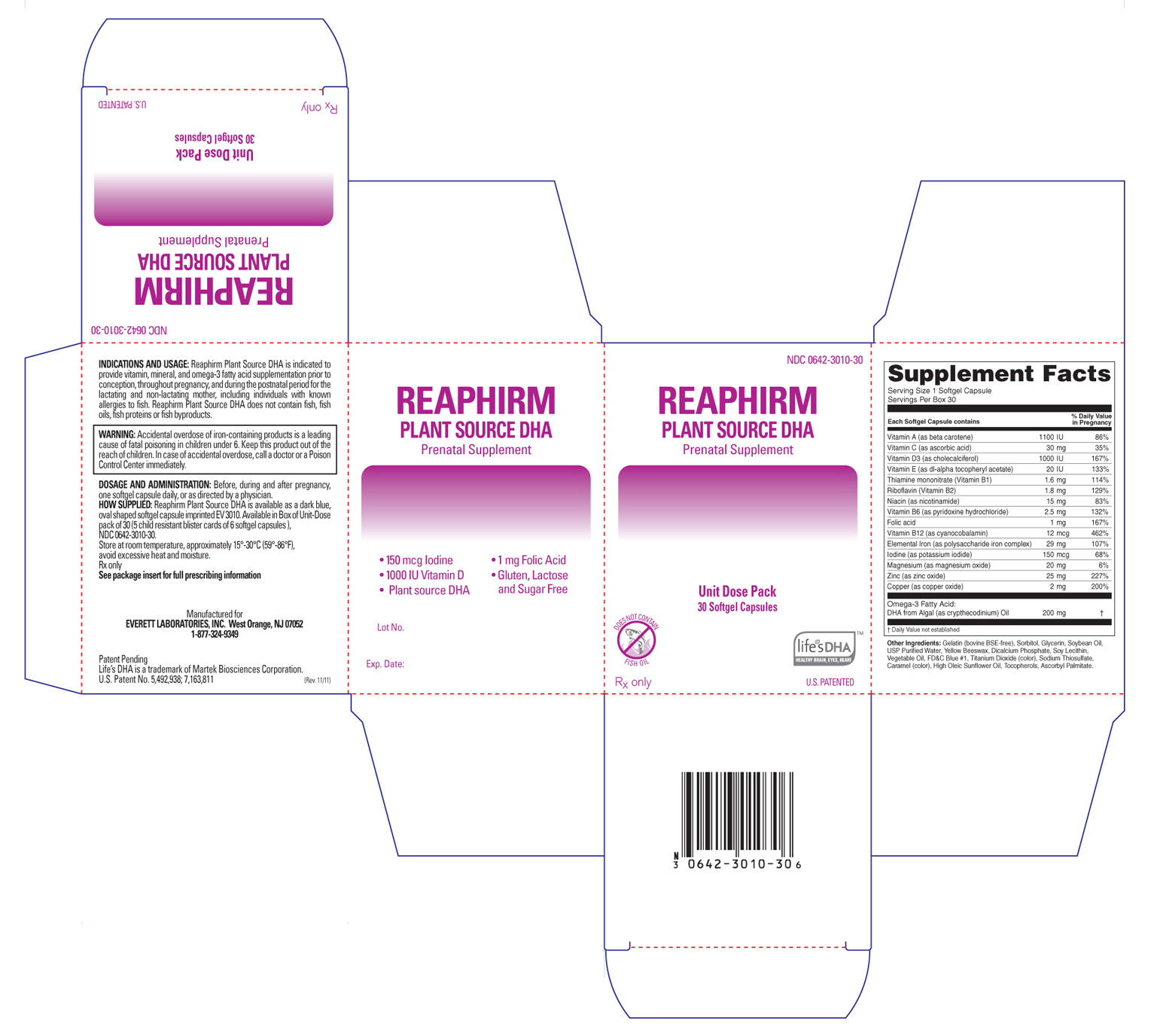 DRUG LABEL: Reaphirm Plant Source DHA
NDC: 0642-3010 | Form: CAPSULE, GELATIN COATED
Manufacturer: Everett Laboratories, Inc.
Category: prescription | Type: HUMAN PRESCRIPTION DRUG LABEL
Date: 20111128

ACTIVE INGREDIENTS: Vitamin A 1100 [iU]/1 1; Ascorbic Acid 30 mg/1 1; Thiamine Mononitrate  1.6 mg/1 1; Riboflavin 1.8 mg/1 1; Niacin 15 mg/1 1; Pyridoxine Hydrochloride 2.5  mg/1 1; Cyanocobalamin .012 mg/1 1; Folic Acid 1 mg/1 1; Iodine 0.150 mg/1 1; Magnesium  20 mg/1 1; Zinc  25 mg/1 1; Copper 2 mg/1 1; Vitamin D 1000 [iU]/1 1; Omega-3 Fatty Acids 200 mg/1 1; Vitamin E 20 [iU]/1 1; Iron 29 mg/1 1
INACTIVE INGREDIENTS: Gelatin; Sorbitol; Glycerin; Soybean Oil; Water; Yellow Wax; Anhydrous Dibasic Calcium Phosphate; Lecithin, Soybean; Titanium Dioxide; Sodium Thiosulfate; Sunflower Oil; Tocopherol; Ascorbyl palmitate; Caramel ; FD&C Blue NO. 1; Corn Oil

Product Information.

Contraindications

Reaphirm Plant Source DHA is contraindicated in patients with hypersensitivity to any of its components or color additives.

Folic acid is contraindicated in patients with untreated and uncomplicated pernicious anemia, and in those with anaphylactic sensitivity to folic acid.

Iron Therapy is contraindicated in patients with hemochromatosis and patients with iron storage disease or the potential for iron storage disease due to chronic hemolytic anemia (e.g., inherited anomalies of hemoglobin structure or synthesis and/or red cell enzyme deficiencies, etc.), pyridoxine responsive anemia, or cirrhosis of the liver.

Cyanocobalamin is contraindicated in patients with sensitivity to cobalt or to cyanocobalamin (Vitamin B12).

Refer to MM1carton label

Boxed Warning

WARNING: Accidental overdose of iron-containing products is a leading cause of fatal poisoning in children under 6. Keep this product out of the reach of children. In case of accidental overdose, call a doctor or a Poison Control Center immediately.

WARNINGS/PRECAUTIONS:

Reaphirm Plant Source DHA should be used with caution in patients with known sensitivity or allergy to soy.
Vitamin D supplementation should be used with caution in those with hypercalcemia or conditions that may lead to hypercalcemia such as hyperparathyroidism and those who form calcium-containing kigney stones. High doses of vitamin D can lead to elevated levels of calcium that reside in the blood and soft tissues. Bone pain, high blood pressure, formation of kidney stones, renal failure, and increased risk of heart disease can occur.
Iodine should be used with caution in patients with an overactive thyroid.
Prolonged use of iron salts may produce iron storage disease.
Folic acid, especially in doses above 0.1 mg daily, may obscure pernicious anemia, in that hematologic remission may occur while neurological manifestations remain progressive.
The use of folic acid doses above 1 mg daily may precipitate or exacerbate the neurological damage of vitamin B12 deficiency.
Consumption of more than 3 grams of omega-3 fatty acids per day from all sources may lead to excessive bleeding. Supplemental intake of omega-3 fatty acids such as DHA exceeding 2 grams per day is not recommended.
Avoid Overdosage. Keep out of the reach of children.
Drug Interactions:
Medications for an overactive thyroid (anti-thyroid drugs) used in conjunction with iodine supplementation may lead to hypothyroidism.
Medications for hypertension used in conjunction with iodine supplementation may increase potassium.
High doses of folic acid may result in decreased serum levels of the anticonvulsant drugs.
Vitamin D supplementation should not be given with large amounts of calcium in those with hypercalcemia or conditions that may lead to hypercalcemia such as hyperparathyroidism and those who form calcium-containing kidney stones.
Zinc can inhibit the absorption of certain antibiotics; take at least 2 hours apart to minimize interactions.
Consult appropriate references for additional specific vitamin-drug interactions.
Information for Patients: Patients should be counseled to disclose all medical conditions, including use of all medications, vitamins and supplements, pregnancy, and breast-feeding.
Pediatric Use: Not for pediatric use.

Adverse Reactions

Adverse reactions have been reported with specific vitamins and minerals, but generally at doses substantially higher than those in Reaphirm Plant Source DHA. Reported adverse events include skin ailments, gastrointestinal complaints, glucose abnormalities, and visual problems.

Dosage and Administration

Before, during and after pregnancy, one softgel capsule daily, or as directed by a physician.

How Supplied

Reaphirm Plant Source DHA is available as a dark blue, oval shaped softgel capsule imprinted "EV3010". Available in Box of Unit-Dose pack of 30 (5 child resistant blister cards of 6 softgel capsules).

Store at room temperature, approximately 15-30C (59-86F), avoid excessive heat.

Rx Only

Manufactured for

EVERETT LABORATORIES, INC.

West Orange, NJ 07052

1-877-324-9349

Principal Display Panel

reaphirm111128carton_lcr